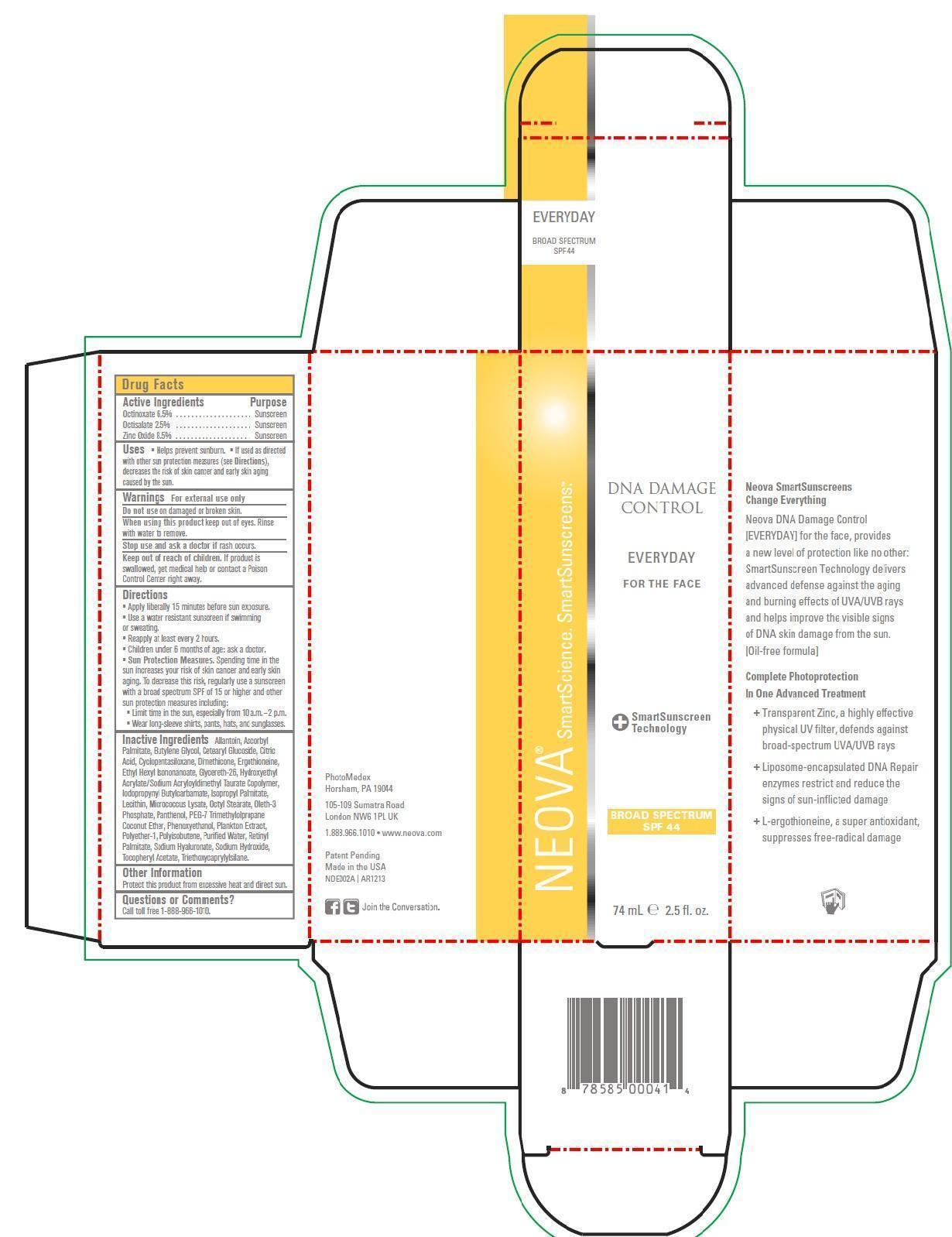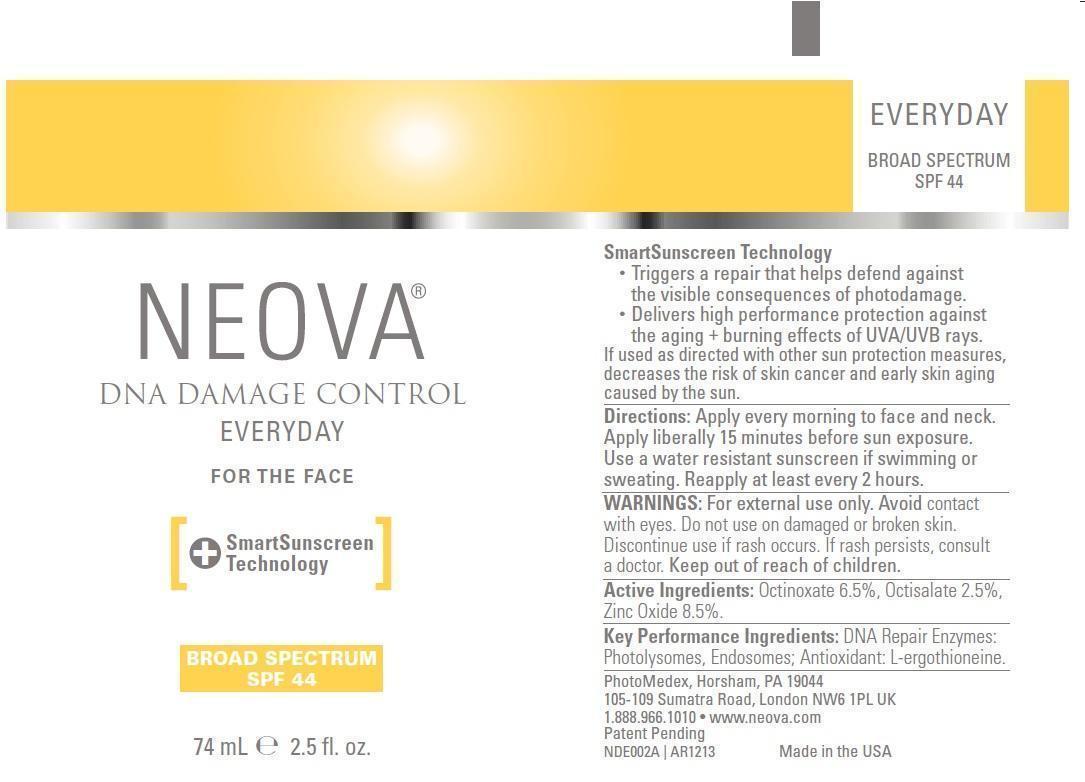 DRUG LABEL: Neova DNA Damage Control - Everyday
NDC: 62362-159 | Form: EMULSION
Manufacturer: PhotoMedex, Inc.
Category: otc | Type: HUMAN OTC DRUG LABEL
Date: 20140102

ACTIVE INGREDIENTS: Octinoxate 6.5 g/100 mL; Octisalate 2.5 g/100 mL; Zinc Oxide 8.5 g/100 mL
INACTIVE INGREDIENTS: Allantoin; Ascorbyl Palmitate; Butylene Glycol; Cetearyl Glucoside; Citric Acid Monohydrate; Cyclomethicone 5; Dimethicone; Ergothioneine; Ethylhexyl Isononanoate; Glycereth-26; Hydroxyethyl Acrylate/Sodium Acryloyldimethyl Taurate Copolymer (45000 MPA.S AT 1%); Iodopropynyl Butylcarbamate; Isopropyl Palmitate; Egg Phospholipids; Octyl Stearate; Oleth-3 Phosphate; Panthenol; Phenoxyethanol; Water; Vitamin A Palmitate; Hyaluronate Sodium; Sodium Hydroxide; .Alpha.-Tocopherol Acetate; Triethoxycaprylylsilane

Neova DNA Damage Control - Everyday SPF 44 - Drug Facts

Active Ingredients

Octinoxate 6.5%, Octisalate 2.5% Zinc Oxide 8.5%

Purpose

Sunscreen

Uses

- Helps prevent sunburn
- If used as directed and with other sun protection measures (see Directions), decreases the risk of skin cancer and early skin again caused by the sun.

Warnings

For external use only

Do not use on damaged or broken skin.

When using this product keep out of eyes. Rinse with water to remove.

Stop use and ask a doctor if rash occurs.

Keep out of reach of children. If product is swallowed, get medical help or contact a Poison Control Center right away.

Directions

- Apply liberally 15 minutes before sun exposure.
- Use a water resistant sunscreen if swimming or sweating.
- Reapply at least every 2 hours.
- Children under 6 months of age: ask a doctor.
- Sun Protection Measures. Spending time in the sun increases your risk of skin cancer and early skin aging. To decrease this risk, regularly use a sunscreen with a broad spectrum SPF of 15 or higher and other sun protection measures including:

°Limit time in the sun, especially from 10 a.m. - 2 p.m.

°Wear long-sleeve shirts, pants, hats, and sunglasses.

Inactive Ingredients

Allantoin, Ascorbyl Palmitate, Butylene Glycol, Cetearyl Glucoside, Citric Acid, Cyclopentasiloxane, Dimethicone, Ergothioneine, Ethyl Hexyl Isononanoate, Glycereth-26, Hydroxyethyl Acrylate/Sodium Acryloyldimethyl Taurate Copolymer, Iodopropynyl Butylcarbamate, Isopropyl Palmitate, Lecithin, Micrococcus Lysate, Octyl Sterate, Oleth-3 Phosphate, Panthenol, PEG-7 Trimethylolprpopane Coconut Ether, Phenoxyethanol, Plankton Extract, Polyether-1, Polyisobutene, Purified Water, Retinyl Palmitate, Sodium Hyaluronate, Sodium Hydroxide, Tocopherol Acetate, Triethoxycaprylysilane.

Other Information

Protect this product from excessive heat and direct sun.

Questions or Comments?

Call toll free 1-888-966-1010.

Neova DNA Damage Control Everyday SPF 44 2.5 fl. oz. (74mL) label and box

DNADamageControlEveryday2-5ozLabel.jpg DNADamageControlEveryday2-5ozBox.jpg